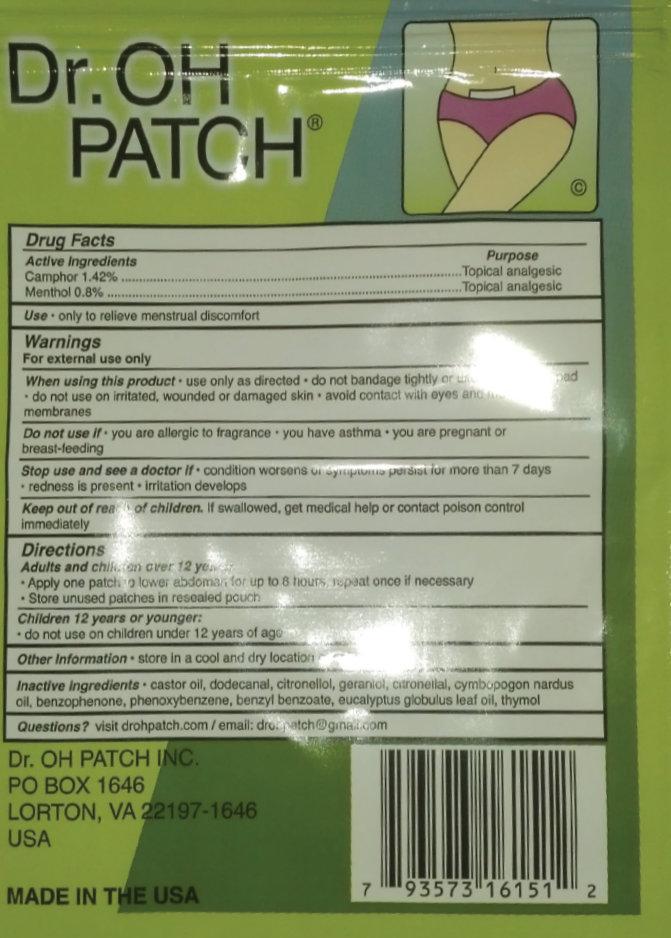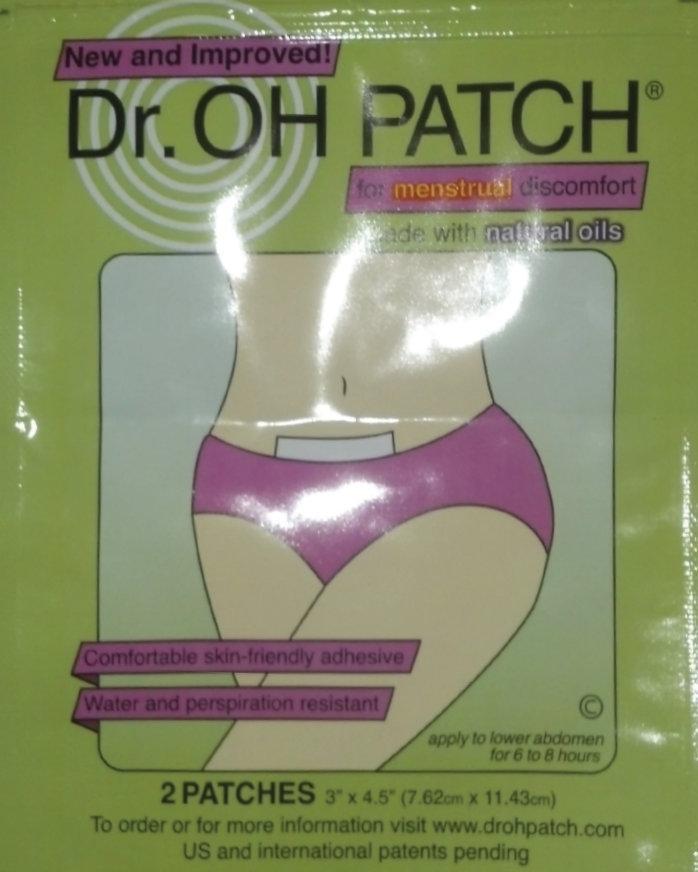 DRUG LABEL: Dr. OH PATCH
NDC: 57541-000 | Form: SOLUTION
Manufacturer: Dr. Oh Patch Inc.
Category: otc | Type: HUMAN OTC DRUG LABEL
Date: 20131119

ACTIVE INGREDIENTS: CAMPHOR (NATURAL) 1.42 mg/100 mg; MENTHOL 0.8 mg/100 mg
INACTIVE INGREDIENTS: CASTOR OIL; LAURYL ALDEHYDE; .BETA.-CITRONELLOL, (R)-; GERANIOL; CITRONELLAL; CITRONELLA OIL; BENZOPHENONE; BENZYL BENZOATE; EUCALYPTUS OIL; THYMOL

Dr. OH PATCH

Active ingredients

Camphor 1.42%
Menthol 0.8%

PURPOSE

Topical Analgesic

Use

Only to relieve menstrual discomforts

Warnings

For external use only

When using this product

- use only as directed
- do not bandage tightly or use with a heating pad
- do not use on irritated, wounded or damaged skin
- avoid contact with eye or mucous membranes

Do not use if

- you are allergic to fragrance
- you have asthma
- you are pregnant or breast-feeding

Stop use and ask a doctor if

- condition worsens or symptoms persist for more than 7 days
- redness is present
- irritation develops

Keep out of reach of children

If patch is swallowed, get medical help or contact poison control center immediately.

Directions

Adults and children over 12 years:

- use only as directed
- use up to 8 hours, repeat once if necessary
- reseal pouch containing unused patches

Children 12 years or younger

- do not use on children under 12 years of age

Other information

- store in a cool and dry location out of direct sunlight

Inactive ingredients

castor oil, dodecanal, citronellol, geraniol, citronellal, cymbopogon nardus oil, benzophenone, phenoxybenzene, benzyl benzoate, eucalyptus globulus leaf oil, thymol

Questions?

visit www.dropatch.com / E-mail: drohpatch@gmail.com

Dr. OH PATCH INC. PO BOX 1646 LORTON, VA 22197-1646 USA MADE IN THE USA To order or for more information visit www.drohpatch.com US and international patents pending

PACKAGE LABEL

New and Improved! Dr. OH PATCH for menstrual discomfort made with natural oils Comfortable skin-friendly adhesive Water and perspiration resistant apply to lower abdomen for 6 to 8 hours 2 PATCHES 3" x 4.5" (7.62cm x 11.43cm)